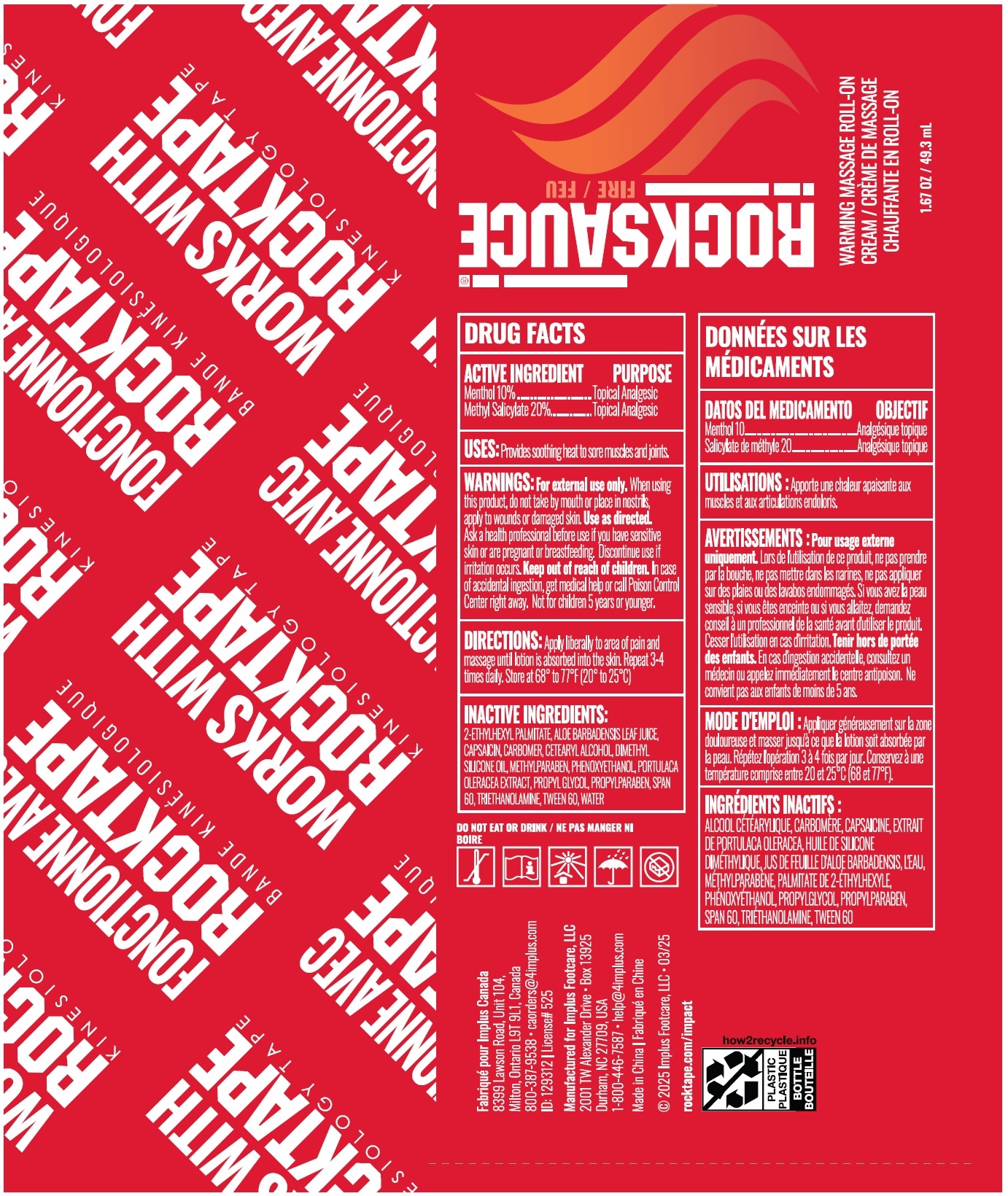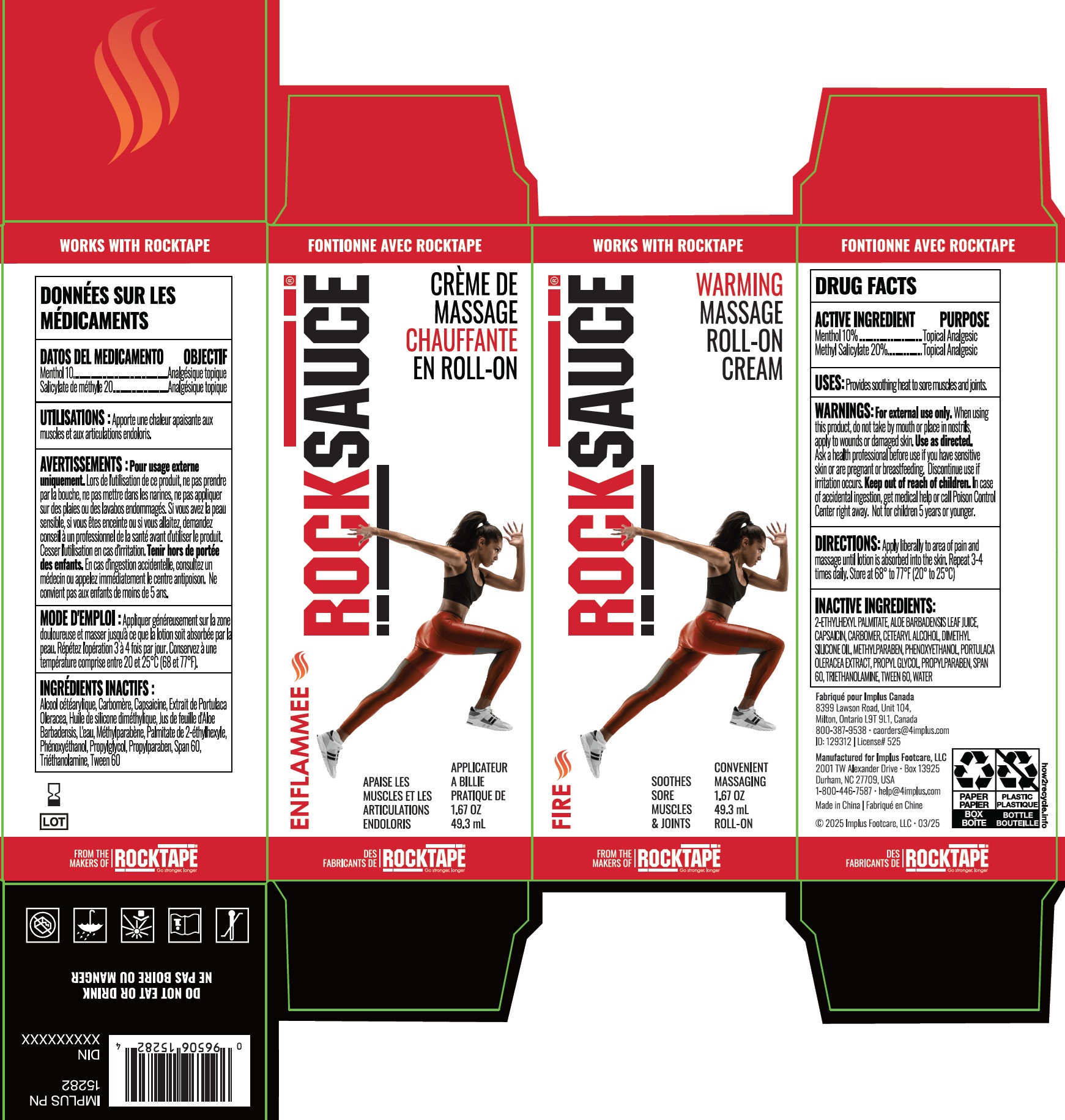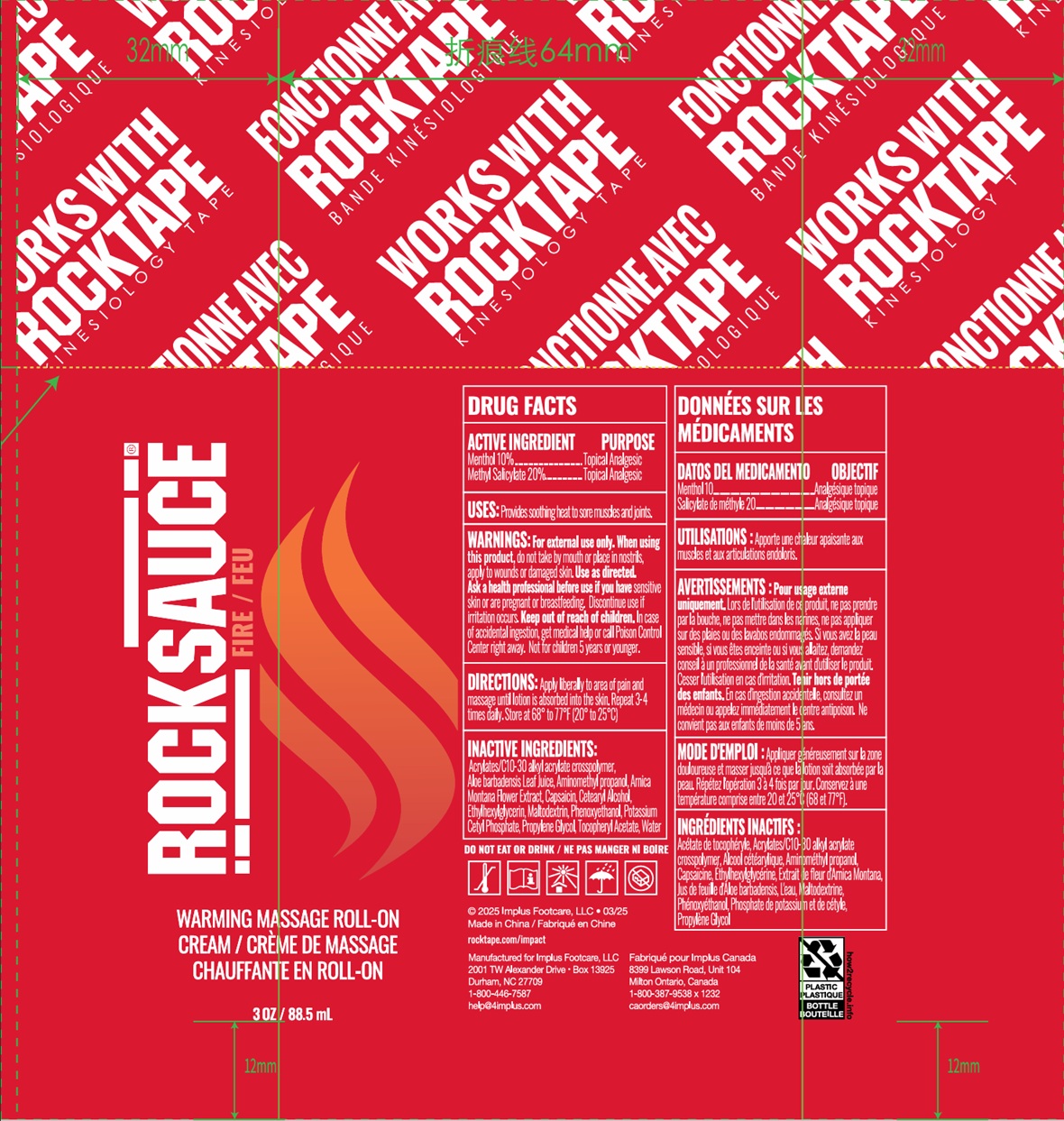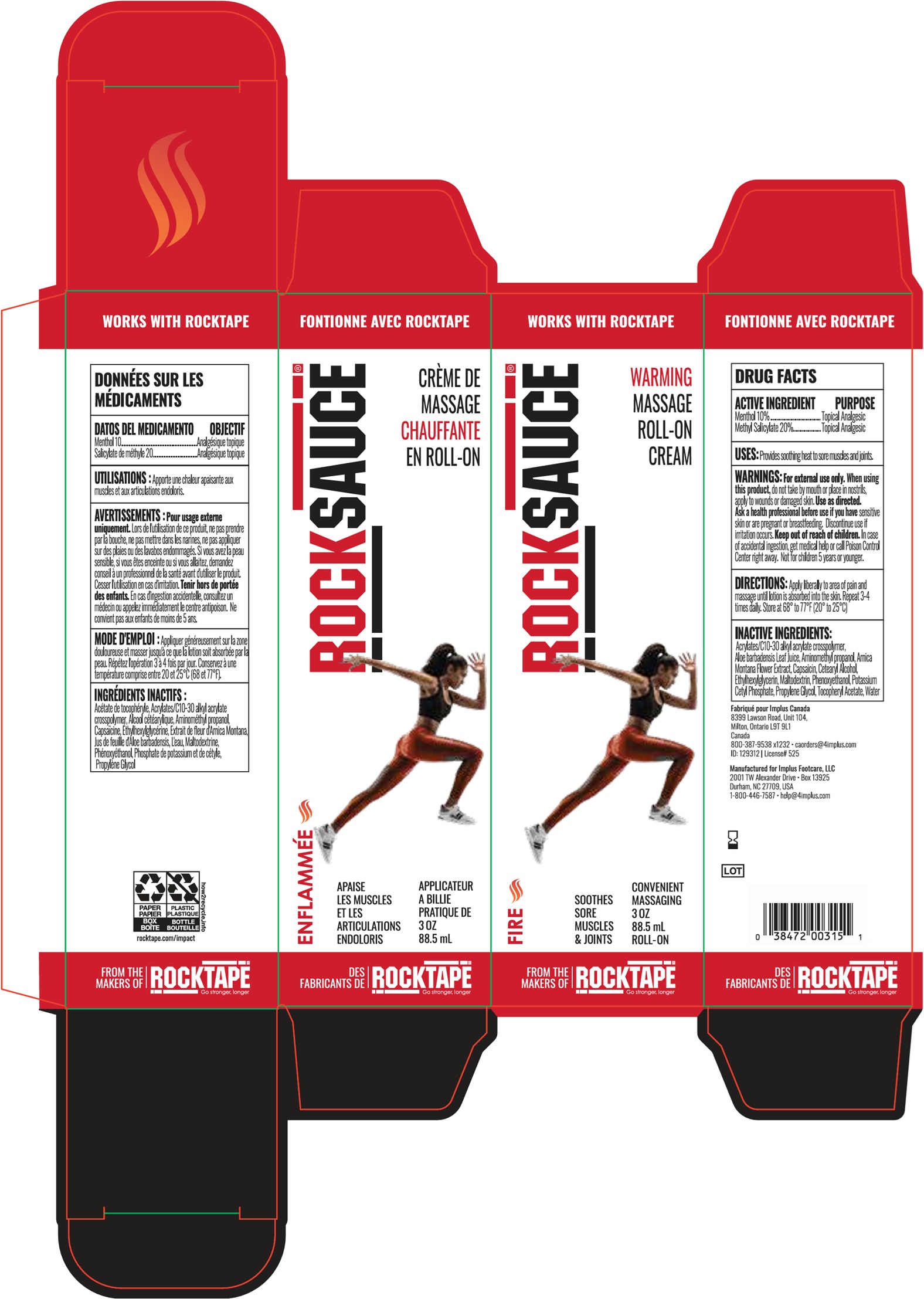 DRUG LABEL: RockSauce Warming Massage Roll-On
NDC: 81683-005 | Form: CREAM, AUGMENTED
Manufacturer: Implus Footcare, LLC
Category: otc | Type: HUMAN OTC DRUG LABEL
Date: 20260129

ACTIVE INGREDIENTS: METHYL SALICYLATE 200 mg/1 mL; MENTHOL 100 mg/1 mL
INACTIVE INGREDIENTS: ARNICA MONTANA FLOWER; AMINOMETHYLPROPANOL; ALOE VERA LEAF JUICE; CAPSAICIN; CARBOMER HOMOPOLYMER, UNSPECIFIED TYPE; CETEARYL ALCOHOL; DIMETHICONE, UNSPECIFIED; METHYLPARABEN; PHENOXYETHANOL; PURSLANE; PROPYLPARABEN; SORBITAN MONOSTEARATE; TROLAMINE; POLYSORBATE 60; WATER

RockSauce Warming Massage Roll-On Cream

ACTIVE INGREDIENT

Menthol 10%

Methyl Salicylate 20%

PURPOSE

Topical Analgesic

USES:

Provides soothing heat to sore muscles and joints.

WARNINGS:

For external use only.

When using this product,

do not take by mouth or pace in nostrils, apply to wounds or damaged skin. Use as directed.

Ask a health professional before use

if you have senstive skin or are pregnant or breastfeeding. Discontinue use if irritation occurs.

Keep out of reach of children.

In case of accidental ingestion, get medical help or call Poison Control Center right away. Not for children 5 years or youger.

DIRECTIONS:

Apply liberally to area of pain and massage until lotion is absorbed into the skin. Repeat 3-4 times daily. Store at 68°to 77°F (20° to 25°C)

Inactive Ingredients NDC: 81683-005-01

2-ETHYLHEXYL PALAMITATE, ALOE BARBADENSIS LEAF JUICE, CAPSAICIN, CARBOMER, CETEARYL ALCOHOL, DIMETHYL SILICONE OIL, METHYLPARABEN, PHENOXYETHANOL, PORTULACA OLERACEA EXTRACT, PROPYL GLYCOL, PROPYLPARABEN, SPAN 60, TRIETHANOLAMINE, TWEEN 60, WATER

Inactive Ingredients NDC: 81683-005-02

Acrylates/C10-30 alkyl acrylate crosspolymer, Aloe barbadensis Leaf Juice, Aminomethyl propanol, Arnica Montana Flower Extract, Capsaicin, Cetearyl Alcohol, Ethylhexylglycerin, Maltodextrin, Phenoxyethanol, Potassium Cetyl Phosphate, Propylene Glycol, Tocopheryl Acetate, Water